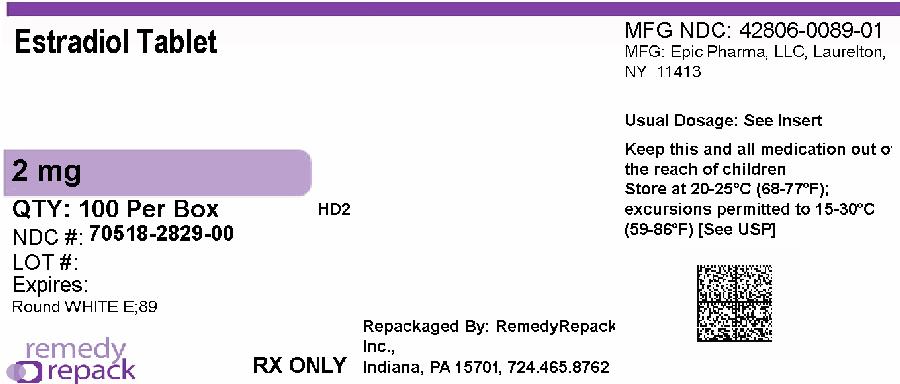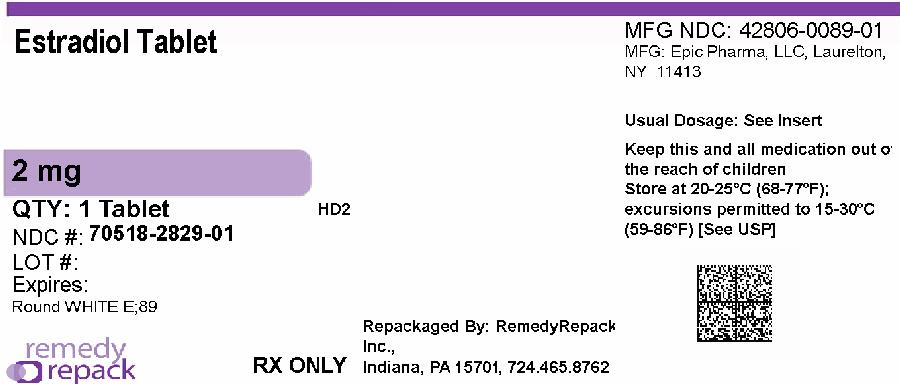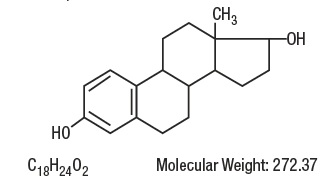 DRUG LABEL: ESTRADIOL
NDC: 70518-2829 | Form: TABLET
Manufacturer: REMEDYREPACK INC.
Category: prescription | Type: HUMAN PRESCRIPTION DRUG LABEL
Date: 20260213

ACTIVE INGREDIENTS: ESTRADIOL 2 mg/1 1
INACTIVE INGREDIENTS: MICROCRYSTALLINE CELLULOSE; SODIUM STARCH GLYCOLATE TYPE A POTATO; MAGNESIUM STEARATE; LACTOSE MONOHYDRATE

Estradiol Tablets, USP

BOXED WARNING

ESTROGENS INCREASE THE RISK OF ENDOMETRIAL CANCER

Close clinical surveillance of all women taking estrogens is important. Adequate diagnostic measures, including endometrial sampling when indicated, should be undertaken to rule out malignancy in all cases of undiagnosed persistent or recurring abnormal vaginal bleeding. There is no evidence that the use of “natural” estrogens results in a different endometrial risk profile than “synthetic” estrogens at equivalent estrogen doses (See WARNINGS, Malignant neoplasms, Endometrial cancer).

CARDIOVASCULAR AND OTHER RISKS

Estrogens with or without progestins should not be used for the prevention of cardiovascular disease (See WARNINGS, Cardiovascular disorders).

The Women’s Health Initiative (WHI) study reported increased risks of myocardial infarction, stroke, invasive breast cancer, pulmonary emboli, and deep vein thrombosis in postmenopausal women (50 to 79 years of age) during 5 years of treatment with oral conjugated estrogens (CE 0.625 mg) combined with medroxyprogesterone acetate (MPA 2.5 mg) relative to placebo (See CLINICAL PHARMACOLOGY, Clinical Studies).

The Women’s Health Initiative Memory Study (WHIMS), a substudy of WHI, reported increased risk of developing probable dementia in postmenopausal women 65 years of age or older during 4 years of treatment with oral conjugated estrogens plus medroxyprogesterone acetate relative to placebo. It is unknown whether this finding applies to younger postmenopausal women or to women taking estrogen alone therapy (See CLINICAL PHARMACOLOGY, Clinical Studies).

Other doses of oral conjugated estrogens with medroxyprogesterone acetate, and other combinations and dosage forms of estrogens and progestins were not studied in the WHI clinical trials and, in the absence of comparable data, these risks should be assumed to be similar. Because of these risks, estrogens with or without progestins should be prescribed at the lowest effective doses and for the shortest duration consistent with treatment goals and risks for the individual woman.

DESCRIPTION

Estradiol tablets, USP for oral administration contains 0.5, 1 or 2 mg of micronized estradiol, USP per tablet.

Estradiol, USP (17β-estradiol) is a white, crystalline solid, chemically described as estra-1,3,5,(10)-triene-3, 17β-diol. The structural formula is:

In addition, each tablet for oral administration contains the following inactive ingredients: lactose monohydrate, magnesium stearate, microcrystalline cellulose and sodium starch glycolate.

CLINICAL PHARMACOLOGY

Endogenous estrogens are largely responsible for the development and maintenance of the female reproductive system and secondary sexual characteristics. Although circulating estrogens exist in a dynamic equilibrium of metabolic interconversions, estradiol is the principal intracellular human estrogen and is substantially more potent than its metabolites, estrone and estriol at the receptor level.

The primary source of estrogen in normally cycling adult women is the ovarian follicle, which secretes 70 to 500 mcg of estradiol daily, depending on the phase of the menstrual cycle. After menopause, most endogenous estrogen is produced by conversion of androstenedione, secreted by the adrenal cortex, to estrone by peripheral tissues. Thus, estrone and the sulfate conjugated form, estrone sulfate, are the most abundant circulating estrogens in postmenopausal women.

Estrogens act through binding to nuclear receptors in estrogen-responsive tissues. To date, two estrogen receptors have been identified. These vary in proportion from tissue to tissue.

Circulating estrogens modulate the pituitary secretion of the gonadotropins, luteinizing hormone (LH) and follicle stimulating hormone (FSH), through a negative feedback mechanism. Estrogens act to reduce the elevated levels of these hormones seen in postmenopausal women.

Pharmacokinetics

Distribution

The distribution of exogenous estrogens is similar to that of endogenous estrogens. Estrogens are widely distributed in the body and are generally found in higher concentrations in the sex hormone target organs. Estrogens circulate in the blood largely bound to sex hormone binding globulin (SHBG) and albumin.

Metabolism

Exogenous estrogens are metabolized in the same manner as endogenous estrogens. Circulating estrogens exist in a dynamic equilibrium of metabolic interconversions. These transformations take place mainly in the liver. Estradiol is converted reversibly to estrone, and both can be converted to estriol, which is the major urinary metabolite. Estrogens also undergo enterohepatic recirculation via sulfate and glucuronide conjugation in the liver, biliary secretion of conjugates into the intestine, and hydrolysis in the gut followed by reabsorption. In postmenopausal women, a significant proportion of the circulating estrogens exist as sulfate conjugates, especially estrone sulfate, which serves as a circulating reservoir for the formation of more active estrogens.

Excretion

Estradiol, estrone, and estriol are excreted in the urine along with glucuronide and sulfate conjugates.

Special Populations

No pharmacokinetic studies were conducted in special populations, including patients with renal or hepatic impairment.

Drug Interactions

In vitroand in vivostudies have shown that estrogens are metabolized partially by cytochrome P450 3A4 (CYP3A4). Therefore, inducers or inhibitors of CYP3A4 may affect estrogen drug metabolism. Inducers of CYP3A4 such as St. John’s Wort preparations (Hypericum perforatum), phenobarbital, carbamazepine, and rifampin may reduce plasma concentrations of estrogens, possibly resulting in a decrease in therapeutic effects and/or changes in the uterine bleeding profile. Inhibitors of CYP3A4 such as erythromycin, clarithromycin, ketoconazole, itraconazole, ritonavir and grapefruit juice may increase plasma concentrations of estrogens and may result in side effects.

Clinical Studies

Osteoporosis

Most prospective studies of efficacy for this indication have been carried out in white menopausal women, without stratification by other risk factors, and tend to show a universally salutary effect on bone.

The results of a two-year, randomized, placebo-controlled, double-blind, dose-ranging study have shown that treatment with 0.5 mg estradiol daily for 23 days (of a 28 day cycle) prevents vertebral bone mass loss in postmenopausal women. When estrogen therapy is discontinued, bone mass declines at a rate comparable to the immediate postmenopausal period. There is no evidence that estrogen replacement therapy restores bone mass to premenopausal levels.

Women’s Health Initiative Studies

The Women’s Health Initiative (WHI) enrolled a total of 27,000 predominantly healthy postmenopausal women to assess the risks and benefits of either the use of oral 0.625 mg conjugated estrogens (CE) per day alone or the use of oral 0.625 mg conjugated estrogens plus 2.5 mg medroxyprogesterone acetate (MPA) per day compared to placebo in the prevention of certain chronic diseases. The primary endpoint was the incidence of coronary heart disease (CHD) (nonfatal myocardial infarction and CHD death), with invasive breast cancer as the primary adverse outcome studied. A “global index” included the earliest occurrence of CHD, invasive breast cancer, stroke, pulmonary embolism (PE), endometrial cancer, colorectal cancer, hip fracture, or death due to other cause. The study did not evaluate the effects of CE or CE/MPA on menopausal symptoms.

The CE/MPA substudy was stopped early because, according to the predefined stopping rule, the increased risk of breast cancer and cardiovascular events exceeded the specified benefits included in the “global index.” Results of the CE/MPA substudy, which included 16,608 women (average age of 63 years, range 50 to 79; 83.9% White, 6.5% Black, 5.5% Hispanic), after an average follow-up of 5.2 years are presented in Table 1 below:

Table 1: RELATIVE AND ABSOLUTE RISK SEEN IN THE CE/MPA SUBSTUDY OF WHI^1

Event^2 | Relative Risk; CE/MPA vs placebo; at 5.2 Years; (95% CI^3) | Placebo; n = 8102 | CE/MPA; n = 8506
 |  | Absolute Risk per 10,000; Women-Years
CHD events Non-fatal MI CHD death | 1.29 (1.02 to 1.63); 1.32 (1.02 to 1.72); 1.18 (0.70 to 1.97) | 30; 23; 6 | 37; 30; 7
Invasive breast cancer^4 | 1.26 (1 to 1.59) | 30 | 38
Stroke | 1.41 (1.07 to 1.85) | 21 | 29
Pulmonary embolism | 2.13 (1.39 to 3.25) | 8 | 16
Colorectal cancer | 0.63 (0.43 to 0.92) | 16 | 10
Endometrial cancer | 0.83 (0.47 to 1.47) | 6 | 5
Hip fracture | 0.66 (0.45 to 0.98) | 15 | 10
Death due to causes other than the events above | 0.92 (0.74 to 1.14) | 40 | 37
Global Index^2 | 1.15 (1.03 to 1.28) | 151 | 170
Deep vein thrombosis^5 | 2.07 (1.49 to 2.87) | 13 | 26
Vertebral fractures^5 | 0.66 (0.44 to 0.98) | 15 | 9
Other osteoporotic fractures^5 | 0.77 (0.69 to 0.86) | 170 | 131

^1adapted from JAMA, 2002; 288:321-333

^2a subset of the events was combined in a “global index”, defined as the earliest occurrence of CHD events, invasive breast cancer, stroke, pulmonary embolism, endometrial cancer, colorectal cancer, hip fracture, or death due to other causes

^3nominal confidence intervals unadjusted for multiple looks and multiple comparisons

^4includes metastatic and non-metastatic breast cancer with the exception of in situ breast cancer

^5not included in Global Index

For those outcomes included in the “global index,” the absolute excess risks per 10,000 women-years in the group treated with CE/MPA were 7 more CHD events, 8 more strokes, 8 more PEs, and 8 more invasive breast cancers, while the absolute risk reductions per 10,000 women-years were 6 fewer colorectal cancers and 5 fewer hip fractures. The absolute excess risk of events included in the “global index” was 19 per 10,000 women-years. There was no difference between the groups in terms of all-cause mortality (See BOXED WARNINGS, WARNINGS, and PRECAUTIONS).

Women’s Health Initiative Memory Study

The Women’s Health Initiative Memory Study (WHIMS), a substudy of WHI, enrolled 4,532 predominantly healthy postmenopausal women 65 years of age and older (47% were age 65 to 69 years, 35% were 70 to 74 years, and 18% were 75 years of age and older) to evaluate the effects of CE/MPA (0.625 mg conjugated estrogens plus 2.5 mg medroxyprogesterone acetate) on the incidence of probable dementia (primary outcome) compared with placebo.

After an average follow-up of 4 years, 40 women in the estrogen/progestin group (45 per 10,000 women-years) and 21 in the placebo group (22 per 10,000 women-years) were diagnosed with probable dementia. The relative risk of probable dementia in the hormone therapy group was 2.05 (95% CI, 1.21 to 3.48) compared to placebo. Differences between groups became apparent in the first year of treatment. It is unknown whether these findings apply to younger postmenopausal women (See BOXED WARNINGand WARNINGS, Dementia).

INDICATIONS AND USAGE

Estradiol tablets are indicated in the:

1. Treatment of moderate to severe vasomotor symptoms associated with the menopause.
2. Treatment of moderate to severe symptoms of vulvar and vaginal atrophy associated with the menopause. When prescribing solely for the treatment of symptoms of vulvar and vaginal atrophy, topical vaginal products should be considered.
3. Treatment of hypoestrogenism due to hypogonadism, castration or primary ovarian failure.
4. Treatment of breast cancer (for palliation only) in appropriately selected women and men with metastatic disease.
5. Treatment of advanced androgen-dependent carcinoma of the prostate (for palliation only).
6. Prevention of osteoporosis. When prescribing solely for the prevention of postmenopausal osteoporosis, therapy should only be considered for women at significant risk of osteoporosis and for whom non-estrogen medications are not considered to be appropriate (See CLINICAL PHARMACOLOGY, Clinical Studies).

The mainstays for decreasing the risk of postmenopausal osteoporosis are weight bearing exercise, adequate calcium and vitamin D intake, and when indicated, pharmacologic therapy. Postmenopausal women require an average of 1500 mg/day of elemental calcium. Therefore, when not contraindicated, calcium supplementation may be helpful for women with suboptimal dietary intake. Vitamin D supplementation of 400 to 800 IU/day may also be required to ensure adequate daily intake in postmenopausal women.

CONTRAINDICATIONS

Estrogens should not be used in individuals with any of the following conditions:

1. Undiagnosed abnormal genital bleeding.
2. Known, suspected or history of cancer of the breast except in appropriately selected patients being treated for metastatic disease.
3. Known or suspected estrogen-dependent neoplasia.
4. Active deep vein thrombosis, pulmonary embolism or history of these conditions.
5. Active or recent (e.g., within the past year) arterial thromboembolic disease (e.g., stroke, myocardial infarction).
6. Liver dysfunction or disease.
7. Estradiol tablets should not be used in patients with known hypersensitivity to its ingredients.
8. Known or suspected pregnancy. There is no indication for estradiol tablets in pregnancy. There appears to be little or no increased risk of birth defects in children born to women who have used estrogens and progestins from oral contraceptives inadvertently during early pregnancy (See PRECAUTIONS).

WARNINGS

See BOXED WARNINGS.

1. Cardiovascular disorders

Estrogen and estrogen/progestin therapy has been associated with an increased risk of cardiovascular events such as myocardial infarction and stroke, as well as venous thrombosis and pulmonary embolism (venous thromboembolism or VTE). Should any of these occur or be suspected estrogens should be discontinued immediately.

Risk factors for arterial vascular disease (e.g., hypertension, diabetes mellitus, tobacco use, hypercholesterolemia, and obesity) and/or venous thromboembolism (e.g., personal history or family history of VTE, obesity, and systemic lupus erythematosus) should be managed appropriately.

a. Coronary heart disease and stroke

In the Women’s Health Initiative (WHI) study, an increase in the number of myocardial infarctions and strokes has been observed in women receiving CE compared to placebo. These observations are preliminary, and the study is continuing (See CLINICAL PHARMACOLOGY, Clinical Studies).

In the CE/MPA substudy of WHI, an increased risk of coronary heart disease (CHD) events (defined as nonfatal myocardial infarction and CHD death) was observed in women receiving CE/MPA compared to women receiving placebo (37 vs 30 per 10,000 women-years). The increase in risk was observed in year one and persisted.

In the same substudy of WHI, an increased risk of stroke was observed in women receiving CE/MPA compared to women receiving placebo (29 vs 21 per 10,000 women-years). The increase in risk was observed after the first year and persisted.

In postmenopausal women with documented heart disease (n = 2,763, average age 66.7 years) a controlled clinical trial of secondary prevention of cardiovascular disease (Heart and Estrogen/Progestin Replacement Study; HERS) treatment with CE/MPA (0.625 mg/2.5 mg per day) demonstrated no cardiovascular benefit. During an average follow-up of 4.1 years, treatment with CE/MPA did not reduce the overall rate of CHD events in postmenopausal women with established coronary heart disease. There were more CHD events in the CE/MPA-treated group than in the placebo group in year 1, but not during the subsequent years. Two thousand three hundred and twenty one women from the original HERS trial agreed to participate in an open label extension of HERS, HERS II. Average follow-up in HERS II was an additional 2.7 years, for a total of 6.8 years overall. Rates of CHD events were comparable among women in the CE/MPA group and the placebo group in HERS, HERS II, and overall.

Large doses of estrogen (5 mg conjugated estrogens per day), comparable to those used to treat cancer of the prostate and breast, have been shown in a large prospective clinical trial in men to increase the risks of nonfatal myocardial infarction, pulmonary embolism, and thrombophlebitis.

b. Venous thromboembolism (VTE)

In the Women’s Health Initiative (WHI) study, an increase in VTE has been observed in women receiving CE compared to placebo. These observations are preliminary, and the study is continuing (See CLINICAL PHARMACOLOGY, Clinical Studies).

In the CE/MPA substudy of WHI, a 2-fold greater rate of VTE, including deep venous thrombosis and pulmonary embolism, was observed in women receiving CE/MPA compared to women receiving placebo. The rate of VTE was 34 per 10,000 women-years in the CE/MPA group compared to 16 per 10,000 women-years in the placebo group. The increase in VTE risk was observed during the first year and persisted.

If feasible, estrogens should be discontinued at least 4 to 6 weeks before surgery of the type associated with an increased risk of thromboembolism, or during periods of prolonged immobilization.

2. Malignant neoplasms

a. Endometrial cancer

The use of unopposed estrogens in women with intact uteri has been associated with an increased risk of endometrial cancer. The reported endometrial cancer risk among unopposed estrogen users is about 2- to 12-fold greater than in non-users, and appears dependent on duration of treatment and on estrogen dose. Most studies show no significant increased risk associated with use of estrogens for less than one year. The greatest risk appears associated with prolonged use with increased risks of 15- to 24-fold for five to ten years or more and this risk persists for 8 to over 15 years after estrogen therapy is discontinued.

Clinical surveillance of all women taking estrogen/progestin combinations is important (see PRECAUTIONS). Adequate diagnostic measures, including endometrial sampling when indicated, should be undertaken to rule out malignancy in all cases of undiagnosed persistent or recurring abnormal vaginal bleeding. There is no evidence that the use of natural estrogens results in a different endometrial risk profile than synthetic estrogens of equivalent estrogen dose. Adding a progestin to estrogen therapy has been shown to reduce the risk of endometrial hyperplasia, which may be a precursor to endometrial cancer.

b. Breast cancer

The most important randomized clinical trial providing information about breast cancer in estrogen plus progestin users is the WHI substudy of daily CE (0.625 mg) plus MPA (2.5 mg). After a mean follow-up of 5.6 years, the estrogen plus progestin substudy reported an increased risk of invasive breast cancer in women who took daily CE plus MPA. In this substudy, prior use of estrogen‑alone or estrogen plus progestin therapy was reported by 26 percent of the women. The relative risk of invasive breast cancer was 1.24, and the absolute risk was 41 versus 33 cases per 10,000 women-years, for CE plus MPA compared with placebo. Among women who reported prior use of hormone therapy, the relative risk of invasive breast cancer was 1.86, and the absolute risk was 46 versus 25 cases per 10,000 women-years, for CE plus MPA compared with placebo. Among women who reported no prior use of hormone therapy, the relative risk of invasive breast cancer was 1.09, and the absolute risk was 40 versus 36 cases per 10,000 women-years, for CE plus MPA compared with placebo. In the same substudy, invasive breast cancers were larger, were more likely to be node positive, and were diagnosed at a more advanced stage in the CE (0.625 mg) plus MPA (2.5 mg) group compared with the placebo group. Metastatic disease was rare, with no apparent difference between the two groups. Other prognostic factors, such as histologic subtype, grade and hormone receptor status did not differ between the groups.:

The most important randomized clinical trial providing information about breast cancer in estrogen-alone users is the WHI substudy of daily CE (0.625 mg)‑alone. In the WHI estrogen-alone substudy, after an average follow-up of 7.1 years, daily CE (0.625 mg)-alone was not associated with an increased risk of invasive breast cancer [relative risk (RR) 0.80].

Consistent with the Women's Health Initiative (WHI clinical trials), observational studies have also reported an increased risk of breast cancer for estrogen plus progestin therapy and a smaller, but still increased risk, for estrogen-alone therapy after several years of use. One large meta-analysis of prospective cohort studies reported increased risks that were dependent upon duration of use and could last up to >10 years after discontinuation of estrogen plus progestin therapy and estrogen-alone therapy. Extension of the WHI trials also demonstrated increased breast cancer risk associated with estrogen plus progestin therapy. Observational studies also suggest that the risk of breast cancer was greater, and became apparent earlier, with estrogen plus progestin therapy as compared to the risk with estrogen-alone therapy. However, these studies have not found significant variation in the risk of breast cancer among different estrogen plus progestin combinations, doses, or routes of administration.

The use of estrogen-alone and estrogen plus progestin has been reported to result in an increase in abnormal mammograms requiring further evaluation. All women should receive yearly breast examinations by a healthcare provider and perform monthly breast self-examinations. In addition, mammography examinations should be scheduled based on patient age, risk factors and prior mammogram results.

c. Ovarian Cancer

The WHI estrogen plus progestin substudy reported a statistically non-significant increased risk of ovarian cancer. After an average follow-up of 5.6 years, the relative risk for ovarian cancer for CE plus MPA versus placebo was 1.58 (95 percent CI, 0.77-3.24).

The absolute risk for CE plus MPA versus placebo was 4 versus 3 cases per 10,000 women-years.

A meta-analysis of 17 prospective and 35 retrospective epidemiology studies found that women who used hormonal therapy for menopausal symptoms had an increased risk for ovarian cancer. The primary analysis, using case-control comparisons, included 12,110 cancer cases from the 17 prospective studies. The relative risks associated with current use of hormonal therapy was 1.41 (95% confidence interval [CI] 1.32 to 1.50); there was no difference in the risk estimates by duration of the exposure (less than 5 years [median of 3 years] vs. greater than 5 years [median of 10 years] of use before the cancer diagnosis). The relative risk associated with combined current and recent use (discontinued use within 5 years before cancer diagnosis) was 1.37 (95% CI 1.27-1.48), and the elevated risk was significant for both estrogen-alone and estrogen plus progestin products. The exact duration of hormone therapy use associated with an increased risk of ovarian cancer, however, is unknown.

3. Dementia

In the Women’s Health Initiative Memory Study (WHIMS), 4,532 generally healthy postmenopausal women 65 years of age and older were studied, of whom 35% were 70 to 74 years of age and 18% were 75 or older. After an average follow-up of 4 years, 40 women being treated with CE/MPA (1.8%, n = 2,229) and 21 women in the placebo group (0.9%, n = 2,303) received diagnoses of probable dementia. The relative risk for CE/MPA versus placebo was 2.05 (95% confidence interval 1.21 – 3.48), and was similar for women with and without histories of menopausal hormone use before WHIMS. The absolute risk of probable dementia for CE/MPA versus placebo was 45 versus 22 cases per 10,000 women-years, and the absolute excess risk for CE/MPA was 23 cases per 10,000 women-years. It is unknown whether these findings apply to younger postmenopausal women (See CLINICAL PHARMACOLOGY, Clinical Studiesand PRECAUTIONS, Geriatric Use).

It is unknown whether these findings apply to estrogen alone therapy.

4. Gallbladder disease

A 2- to 4-fold increase in the risk of gallbladder disease requiring surgery in postmenopausal women receiving estrogens has been reported.

5. Hypercalcemia

Estrogen administration may lead to severe hypercalcemia in patients with breast cancer and bone metastases. If hypercalcemia occurs, use of the drug should be stopped and appropriate measures taken to reduce the serum calcium level.

6. Visual abnormalities

Retinal vascular thrombosis has been reported in patients receiving estrogens. Discontinue medication pending examination if there is sudden partial or complete loss of vision, or a sudden onset of proptosis, diplopia or migraine. If examination reveals papilledema or retinal vascular lesions, estrogens should be permanently discontinued.

PRECAUTIONS

A. General

1. Addition of a progestin when a woman has not had a hysterectomy

Studies of the addition of a progestin for 10 or more days of a cycle of estrogen administration, or daily with estrogen in a continuous regimen, have reported a lowered incidence of endometrial hyperplasia than would be induced by estrogen treatment alone. Endometrial hyperplasia may be a precursor to endometrial cancer.

There are, however, possible risks which may be associated with the use of progestins with estrogens compared to estrogen-alone regimens. These include a possible increased risk of breast cancer.

2. Elevated blood pressure

In a small number of case reports, substantial increases in blood pressure have been attributed to idiosyncratic reactions to estrogens. In a large, randomized, placebo-controlled clinical trial, a generalized effect of estrogens on blood pressure was not seen. Blood pressure should be monitored at regular intervals with estrogen use.

3. Hypertriglyceridemia

In patients with pre-existing hypertriglyceridemia, estrogen therapy may be associated with elevations of plasma triglycerides leading to pancreatitis and other complications.

4. Impaired liver function and past history of cholestatic jaundice

Estrogens may be poorly metabolized in patients with impaired liver function. For patients with a history of cholestatic jaundice associated with past estrogen use or with pregnancy, caution should be exercised and in the case of recurrence, medication should be discontinued.

5. Hypothyroidism

Estrogen administration leads to increased thyroid-binding globulin (TBG) levels. Patients with normal thyroid function can compensate for the increased TBG by making more thyroid hormone, thus maintaining free T4and T3serum concentrations in the normal range. Patients dependent on thyroid hormone replacement therapy who are also receiving estrogens may require increased doses of their thyroid replacement therapy. These patients should have their thyroid function monitored in order to maintain their free thyroid hormone levels in an acceptable range.

6. Fluid retention

Because estrogens may cause some degree of fluid retention, patients with conditions that might be influenced by this factor, such as asthma, epilepsy, migraine, and cardiac or renal dysfunction, warrant careful observation when estrogens are prescribed.

7. Hypocalcemia

Estrogens should be used with caution in individuals with severe hypocalcemia.

8. Exacerbation of endometriosis

Endometriosis may be exacerbated with administration of estrogens. A few cases of malignant transformation of residual endometrial implants have been reported in women treated post-hysterectomy with estrogen alone therapy. For patients known to have residual endometriosis post-hysterectomy, the addition of progestin should be considered.

9. Exacerbation of other conditions

Estrogens may cause an exacerbation of asthma, diabetes mellitus, epilepsy, migraine or porphyria, systemic lupus erythematosus, and hepatic hemangiomas and should be used with caution in women with these conditions.

B. Patient Information

Physicians are advised to discuss the PATIENT INFORMATION leaflet with patients for whom they prescribe Estradiol Tablets.

Repackaged By / Distributed By: RemedyRepack Inc.

625 Kolter Drive, Indiana, PA 15701

(724) 465-8762

C. Laboratory Tests

Estrogen administration should be initiated at the lowest dose approved for the indication and then guided by clinical response rather than by serum hormone levels (e.g., estradiol, FSH) (See DOSAGE AND ADMINISTRATION section).

D. Drug/Laboratory Test Interactions

1. Accelerated prothrombin time, partial thromboplastin time, and platelet aggregation time; increased platelet count; increased factors II, VII antigen, VIII antigen, VIII coagulant activity, IX, X, XII, VII-X complex, II-VII-X complex, and beta-thromboglobulin; decreased levels of anti-factor Xa and antithrombin III, decreased antithrombin III activity; increased levels of fibrinogen and fibrinogen activity; increased plasminogen antigen and activity.
2. Increased thyroid-binding globulin (TBG) leading to increased circulating total thyroid hormone, as measured by protein-bound iodine (PBI), T4levels (by column or by radioimmunoassay) or T3levels by radioimmunoassay. T3resin uptake is decreased, reflecting the elevated TBG. Free T4and free T3concentrations are unaltered. Patients on thyroid replacement therapy may require higher doses of thyroid hormone.
3. Other binding proteins may be elevated in serum, i.e., corticosteroid binding globulin (CBG), sex hormone-binding globulin (SHBG), leading to increased circulating corticosteroids and sex steroids, respectively. Free hormone concentrations may be decreased. Other plasma proteins may be increased (angiotensinogen/renin substrate, alpha-1-antitrypsin, ceruloplasmin).
4. Increased plasma HDL and HDL2subfraction concentrations, reduced LDL cholesterol concentration, increased triglycerides levels.
5. Impaired glucose tolerance.
6. Reduced response to metyrapone test.

E. Carcinogenesis, Mutagenesis, Impairment of Fertility

Long-term continuous administration of estrogen, with and without progestin, in women with and without a uterus, has shown an increased risk of endometrial cancer, breast cancer, and ovarian cancer (See BOXED WARNINGS, WARNINGSand PRECAUTIONS).

Long term continuous administration of natural and synthetic estrogens in certain animal species increases the frequency of carcinomas of the breast, uterus, cervix, vagina, testis, and liver.

F. Pregnancy Category X

Estradiol Tablets should not be used during pregnancy (See CONTRAINDICATIONS).

G. Nursing Mothers

Estrogen administration to nursing mothers has been shown to decrease the quantity and quality of the milk. Detectable amounts of estrogens have been identified in the milk of mothers receiving this drug. Caution should be exercised when estradiol is administered to a nursing woman.

H. Pediatric Use

Safety and effectiveness in pediatric patients have not been established. Large and repeated doses of estrogen over an extended period of time have been shown to accelerate epiphyseal closure, resulting in short adult stature if treatment is initiated before the completion of physiologic puberty in normally developing children. In patients in whom bone growth is not complete, periodic monitoring of bone maturation and effects on epiphyseal centers is recommended.

Estrogen treatment of prepubertal children also induces premature breast development and vaginal cornification, and may potentially induce vaginal bleeding in girls. In boys, estrogen treatment may modify the normal pubertal process. All other physiological and adverse reactions shown to be associated with estrogen treatment of adults could potentially occur in the pediatric population, including thromboembolic disorders and growth stimulation of certain tumors. Therefore, estrogens should only be administered to pediatric patients when clearly indicated and the lowest effective dose should always be utilized.

I. Geriatric Use.

The safety and efficacy of estradiol tablets in geriatric patients has not been established. In general, dose selection for an elderly patient should be cautious, usually starting at the low end of the dosing range, reflecting the greatest frequency of decreased hepatic, renal or cardiac function, and of concomitant disease or other drug therapy.

In the Women’s Health Initiative Memory Study, including 4,532 women 65 years of age and older, followed for an average of 4 years, 82% (n = 3,729) were 65 to 74 while 18% (n = 803) were 75 and over. Most women (80%) had no prior hormone therapy use. Women treated with conjugated estrogens plus medroxyprogesterone acetate were reported to have a two-fold increase in the risk of developing probable dementia. Alzheimer’s disease was the most common classification of probable dementia in both the conjugated estrogens plus medroxyprogesterone acetate group and the placebo group. Ninety percent of the cases of probable dementia occurred in the 54% of women that were older than 70 (See WARNINGS, Dementia).

It is unknown whether these findings apply to estrogen alone therapy.

ADVERSE REACTIONS

See BOXED WARNINGS, WARNINGS, and PRECAUTIONS.

The following additional adverse reactions have been reported with estrogen and/or progestin therapy.

1. Genitourinary system

Changes in vaginal bleeding pattern and abnormal withdrawal bleeding or flow; breakthrough bleeding, spotting, dysmenorrhea

Increase in size of uterine leiomyomata

Vaginitis, including vaginal candidiasis

Change in amount of cervical secretion

Changes in cervical ectropion

Ovarian cancer; endometrial hyperplasia; endometrial cancer

2. Breasts

Tenderness, enlargement, pain, nipple discharge, galactorrhea; fibrocystic breast changes; breast cancer

3. Cardiovascular

Deep and superficial venous thrombosis; pulmonary embolism; thrombophlebitis; myocardial infarction; stroke; increase in blood pressure

4. Gastrointestinal

Nausea, vomiting

Abdominal cramps, bloating

Cholestatic jaundice

Increased incidence of gallbladder disease

Pancreatitis

Enlargement of hepatic hemangiomas

5. Skin

Chloasma or melasma that may persist when drug is discontinued

Erythema multiforme

Erythema nodosum

Hemorrhagic eruption

Loss of scalp hair

Hirsutism

Pruritus, rash

6. Eyes

Retinal vascular thrombosis

Steepening of corneal curvature

Intolerance to contact lenses

7. Central Nervous System

Headache, migraine, dizziness

Mental depression

Chorea

Nervousness, mood disturbances, irritability

Exacerbation of epilepsy

Dementia

8. Miscellaneous

Increase or decrease in weight

Reduced carbohydrate tolerance

Aggravation of porphyria

Edema

Arthralgias; leg cramps

Changes in libido

Urticaria

Angioedema

Anaphylactoid/anaphylactic reactions

Hypocalcemia

Exacerbation of asthma

Increased triglycerides

To report SUSPECTED ADVERSE REACTIONS, contact Epic Pharma, LLC at 1-888-374-2791, or the FDA at 1-800-FDA-1088 or www.fda.gov/ medwatch.

OVERDOSAGE

Serious ill effects have not been reported following acute ingestion of large doses of estrogen-containing oral contraceptives by young children. Overdosage of estrogen may cause nausea and vomiting, and withdrawal bleeding may occur in females.

DOSAGE AND ADMINISTRATION

When estrogen is prescribed for a postmenopausal woman with a uterus, a progestin should also be initiated to reduce the risk of endometrial cancer. A woman without a uterus does not need progestin. Use of estrogen, alone or in combination with a progestin, should be with the lowest effective dose and for the shortest duration consistent with treatment goals and risks for the individual woman. Patients should be reevaluated periodically as clinically appropriate (e.g., 3-month to 6-month intervals) to determine if treatment is still necessary (see BOXED WARNINGSand WARNINGS). For women who have a uterus, adequate diagnostic measures, such as endometrial sampling, when indicated, should be undertaken to rule out malignancy in cases of undiagnosed persistent or recurring abnormal vaginal bleeding.

Patients should be started at the lowest dose for the indication.

1. For treatment of moderate to severe vasomotor symptoms, vulval and vaginal atrophy associated with the menopause, the lowest dose and regimen that will control symptoms should be chosen and medication should be discontinued as promptly as possible.

Attempts to discontinue or taper medication should be made at 3-month to 6-month intervals. The usual initial dosage range is 1 to 2 mg daily of estradiol adjusted as necessary to control presenting symptoms. The minimal effective dose for maintenance therapy should be determined by titration. Administration should be cyclic (e.g., 3 weeks on and 1 week off).

2. For treatment of female hypoestrogenism due to hypogonadism, castration, or primary ovarian failure.

Treatment is usually initiated with a dose of 1 to 2 mg daily of estradiol, adjusted as necessary to control presenting symptoms; the minimal effective dose for maintenance therapy should be determined by titration.

3. For treatment of breast cancer, for palliation only, in appropriately selected women and men with metastatic disease.

Suggested dosage is 10 mg three times daily for a period of at least three months.

4. For treatment of advanced androgen-dependent carcinoma of the prostate, for palliation only.

Suggested dosage is 1 to 2 mg three times daily. The effectiveness of therapy can be judged by phosphatase determinations as well as by symptomatic improvement of the patient.

5. For prevention of osteoporosis.

When prescribing solely for the prevention of postmenopausal osteoporosis, therapy should be considered only for women at significant risk of osteoporosis and for whom non-estrogen medications are not considered to be appropriate.

The lowest effective dose of estradiol has not been determined.

HOW SUPPLIED

Estradiol Tablets, USP, 2 mg are white to off-white, round, convex, bisected tablets, debossed “ Є” above the bisect and “89” below the bisect on one side and plain on the other side.

NDC: 70518-2829-00

NDC: 70518-2829-01

PACKAGING: 100 in 1 BOX

PACKAGING: 1 in 1 POUCH

Store at 20° to 25°C (68° to 77°F) [See USP Controlled Room Temperature].

Dispense contents in a tight, light-resistant container as defined in the USP, with a child-resistant closure, as required.

KEEP THIS AND ALL MEDICATIONS OUT OF THE REACH OF CHILDREN.

Repackaged and Distributed By:

Remedy Repack, Inc.

625 Kolter Dr. Suite #4 Indiana, PA 1-724-465-8762

Patient Information

Estradiol Tablets, USP

Rx Only

Read this PATIENT INFORMATION before you start taking estradiol and read what you get each time you refill estradiol tablets. There may be new information. This information does not take the place of talking to your healthcare provider about your medical condition or your treatment.

WHAT IS THE MOST IMPORTANT INFORMATION I SHOULD KNOW ABOUT ESTRADIOL TABLETS (AN ESTROGEN HORMONE)?

- Estrogens increase the chances of getting cancer of the uterus.

Report any unusual vaginal bleeding right away while you are taking estrogens. Vaginal bleeding after menopause may be a warning sign of cancer of the uterus (womb). Your healthcare provider should check any unusual vaginal bleeding to find out the cause.

- Do not use estrogens with or without progestins to prevent heart disease, heart attacks, or strokes.

Using estrogens with or without progestins may increase your chances of getting heart attacks, strokes, breast cancer, and blood clots. Using estrogens with progestins may increase your risk of dementia. You and your healthcare provider should talk regularly about whether you still need treatment with estradiol tablets.

WHAT ARE ESTRADIOL TABLETS?

Estradiol tablets are medicine that contains estrogen hormones.

WHAT IS ESTRADIOL USED FOR?

Estradiol is used to:

- reduce moderate to severe hot flashes

Estrogens are hormones made by a woman’s ovaries. Between ages 45 and 55, the ovaries normally stop making estrogens. This leads to a drop in body estrogen levels which causes the “change of life” or menopause (the end of monthly menstrual periods). Sometimes, both ovaries are removed during an operation before natural menopause takes place. The sudden drop in estrogen levels causes “surgical menopause.”

When the estrogen levels begin dropping, some women develop very uncomfortable symptoms, such as feelings of warmth in the face, neck, and chest, or sudden strong feelings of heat and sweating (“hot flashes” or “hot flushes”). In some women, the symptoms are mild, and they will not need estrogens. In other women, symptoms can be more severe. You and your healthcare provider should talk regularly about whether you still need treatment with estradiol.

Weight-bearing exercise, like walking or running, and taking calcium with vitamin D supplements may also lower your chances for getting postmenopausal osteoporosis. It is important to talk about exercise and supplements with your healthcare provider before starting them.

- treat dryness, itching, and burning in or around the vagina, difficulty or burning on urination associated with menopause

You and your healthcare provider should talk regularly about whether you still need treatment with estradiol to control these problems. If you use estradiol only to treat your dryness, itching, and burning in and around your vagina, talk with your healthcare provider about whether a topical vaginal product would be better for you.

- treat certain conditions in which a young woman’s ovaries do not produce enough estrogen naturally
- treat certain types of abnormal vaginal bleeding due to hormonal imbalance when your doctor has found no serious cause of the bleeding
- treat certain cancers in special situations, in men and women
- prevent thinning of bones

Osteoporosis from menopause is a thinning of the bones that makes them weaker and easier to break. If you use estradiol only to prevent osteoporosis from menopause, talk with your healthcare provider about whether a different treatment or medicine without estrogens might be better for you. You and your healthcare provider should talk regularly about whether you should continue with estradiol.

WHO SHOULD NOT USE ESTRADIOL?

Do not start taking estradiol if you:

- have unusual vaginal bleeding which has not been evaluated by your doctor (see BOXED WARNINGS)

Unusual vaginal bleeding can be a warning sign of cancer of the uterus, especially if it happens after menopause. Your doctor must find out the cause of the bleeding so that he or she can recommend the proper treatment. Taking estrogens without visiting your doctor can cause you serious harm if your vaginal bleeding is caused by cancer of the uterus.

- currently have or have had certain cancers

Estrogens may increase the risk of certain types of cancer, including cancer of the breast or uterus. If you have or had cancer, talk with your healthcare provider about whether you should take estradiol.

(For certain patients with breast or prostate cancer, estrogens may help.)

- had a stroke or heart attack in the past year
- currently have or have had blood clots
- have or have had liver problems
- are allergic to estradiol tablets or any of its ingredients

See the end of this leaflet for a list of ingredients in estradiol tablets.

- think you may be pregnant

Tell your healthcare provider:

- if you are breast feeding

The hormone in estradiol can pass into your milk

- about all of your medical problems

Your healthcare provider may need to check you more carefully if you have certain conditions, such as asthma (wheezing), epilepsy (seizures), migraine, endometriosis, lupus, problems with your heart, liver, thyroid, kidneys, or have high calcium levels in your blood.

- about all the medicines you take

This includes prescription and nonprescription medicines, vitamins, and herbal supplements. Some medicines may affect how estradiol tablets work. Estradiol tablets may also affect how your other medicines work.

- if you are going to have surgery or will be on bed rest

You may need to stop taking estrogens.

HOW SHOULD I TAKE ESTRADIOL TABLETS?

1. Start at the lowest dose and talk to your healthcare provider about how well that dose is working for you.
2. Estrogens should be used at the lowest dose possible for your treatment only as long as needed. You and your healthcare provider should talk regularly (for example, every 3 to 6 months) about the dose you are taking and whether you still need treatment with estradiol.

WHAT ARE THE POSSIBLE SIDE EFFECTS OF ESTROGENS?

Less common but serious side effects include:

- Breast cancer
- Cancer of the uterus
- Stroke
- Heart attack
- Blood clots
- Dementia
- Gallbladder disease
- Ovarian cancer

These are some of the warning signs of the serious side effects:

- Breast lumps
- Unusual vaginal bleeding
- Dizziness and faintness
- Changes in speech
- Severe headaches
- Chest pain
- Shortness of breath
- Pains in your legs
- Changes in vision
- Vomiting

Call your healthcare provider right away if you get any of these warning signs, or any other unusual symptom that concerns you.

Common side effects include:

- Headache
- Breast pain
- Irregular vaginal bleeding or spotting
- Stomach/abdominal cramps, bloating
- Nausea and vomiting
- Hair loss

Other side effects include:

- High blood pressure
- Liver problems
- High blood sugar
- Fluid retention
- Enlargement of benign tumors (“fibroids”) of the uterus
- A spotty darkening of the skin, particularly on the face
- Vaginal yeast infection

These are not all the possible side effects of estradiol tablets. For more information, ask your healthcare provider or pharmacist.

WHAT CAN I DO TO LOWER MY CHANCES OF A SERIOUS SIDE EFFECT WITH ESTRADIOL?

If you use estrogens, you can reduce your risks by doing these things:

- Talk with your healthcare provider:
- While you are using estrogens, it is important to visit your doctor at least once a year for a check-up.
- If you have a uterus, talk to your healthcare provider about whether the addition of a progestin is right for you.
- See your healthcare provider right away if you have vaginal bleeding while taking estradiol tablets.
- Have a breast exam and mammogram (breast x-ray) every year unless your healthcare provider tells you something else. If members of your family have had breast cancer or if you have ever had breast lumps or an abnormal mammogram (breast x-ray), you may need to have more frequent breast examinations.
- If you have high blood pressure, high cholesterol (fat in the blood), diabetes, are overweight, or if you use tobacco, you may have higher chances for getting heart disease. Ask your healthcare provider for ways to lower your chances for getting heart disease.
- Talk with your healthcare provider regularly about whether you should continue taking estradiol tablets. You and your doctor should reevaluate whether or not you still need estrogens at least every six months.
- Be alert for signs of trouble

If any of these warning signals (or any other unusual symptoms) happen while you are using estrogens, call your doctor immediately:

- Abnormal bleeding from the vagina (possible uterine cancer)
- Pains in the calves or chest, sudden shortness of breath, or coughing blood (possible clot in the legs, or lungs)
- Severe headache or vomiting, dizziness, faintness, changes in vision or speech, weakness or numbness of an arm or leg (possible clot in the brain or eye)
- Breast lumps (possible breast cancer; ask your doctor or health professional to show you how to examine your breasts monthly)
- Yellowing of the skin or eyes (possible liver problem)
- Pain, swelling, or tenderness in the abdomen (possible gallbladder problem)

Call your doctor for medical advice about side effects. You may report side effects to FDA at 1-800-FDA-1088.

GENERAL INFORMATION ABOUT SAFE AND EFFECTIVE USE OF ESTRADIOL TABLETS

Medicines are sometimes prescribed for conditions that are not mentioned in patient information leaflets.

Do not take estradiol tablets for conditions for which they were not prescribed. Do not give estradiol tablets to other people, even if they have the same symptoms you have. They may harm them.

KEEP ESTRADIOL TABLETS OUT OF THE REACH OF CHILDREN

This leaflet provides a summary of the most important information about estradiol tablets. If you would like more information, talk with your healthcare provider or pharmacist. You can ask for information about estradiol tablets that is written for health professionals. For more information about estradiol call Epic Pharma, LLC at 1-888-374-2791.

WHAT ARE THE INGREDIENTS IN ESTRADIOL TABLETS?

Estradiol Tablets USP for oral administration contains 0.5, 1 or 2 mg of estradiol, USP.

In addition, each tablet for oral administration contains the following inactive ingredients: lactose monohydrate, magnesium stearate, microcrystalline cellulose and sodium starch glycolate.

Repackaged and Distributed By:

Remedy Repack, Inc.

625 Kolter Dr. Suite #4 Indiana, PA 1-724-465-8762

PRINCIPAL DISPLAY PANEL

DRUG: ESTRADIOL

GENERIC: ESTRADIOL

DOSAGE: TABLET

ADMINSTRATION: ORAL

NDC: 70518-2829-0

NDC: 70518-2829-1

COLOR: white

SHAPE: ROUND

SCORE: Two even pieces

SIZE: 10 mm

IMPRINT: E;89

PACKAGING: 1 in 1 POUCH

OUTER PACKAGING: 100 in 1 BOX

ACTIVE INGREDIENT(S):

- ESTRADIOL 2mg in 1

INACTIVE INGREDIENT(S):

- LACTOSE MONOHYDRATE
- MICROCRYSTALLINE CELLULOSE
- SODIUM STARCH GLYCOLATE TYPE A POTATO
- MAGNESIUM STEARATE